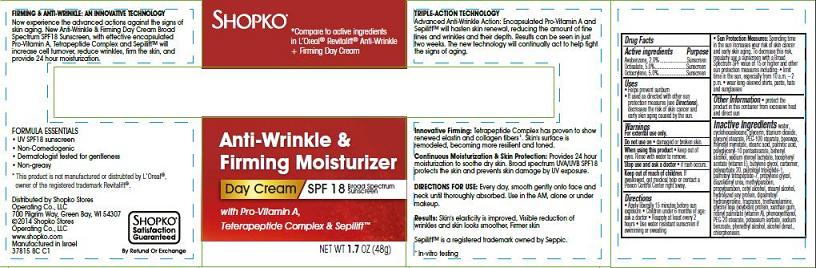 DRUG LABEL: Shopko Anti-Wrinkle and Firming Moisturizer Day Broad Spectrum SPF18
NDC: 37012-815 | Form: CREAM
Manufacturer: Shopko Stores Operating Co., LLC
Category: otc | Type: HUMAN OTC DRUG LABEL
Date: 20140408

ACTIVE INGREDIENTS: AVOBENZONE 2 g/100 g; OCTISALATE 5 g/100 g; OCTOCRYLENE 5 g/100 g
INACTIVE INGREDIENTS: WATER; CYCLOMETHICONE 6; GLYCERIN; TITANIUM DIOXIDE; GLYCERYL MONOSTEARATE; PEG-100 STEARATE; ROYAL JELLY; MYRISTYL MYRISTATE; STEARIC ACID; PALMITIC ACID; POLYGLYCERYL-10 STEARATE; DOCOSANOL; SODIUM STEAROYL LACTYLATE; .ALPHA.-TOCOPHEROL ACETATE; BUTYLENE GLYCOL; POLYSORBATE 20; PALMITOYL TETRAPEPTIDE-7; PROPYLENE GLYCOL; DIAZOLIDINYL UREA; METHYLPARABEN; PROPYLPARABEN; CETYL ALCOHOL; STEARYL ALCOHOL; DIPALMITOYL HYDROXYPROLINE; TROLAMINE; SOY PROTEIN; XANTHAN GUM; VITAMIN A PALMITATE; PHENOXYETHANOL; PEG-20 STEARATE; POTASSIUM SORBATE; SODIUM BENZOATE; PHENYLETHYL ALCOHOL; CHLORPHENESIN; ALCOHOL

SHOPKO® Anti-Wrinkle & Firming Moisturizer

Active ingredient

Avobenzone, 2.0%
Octisalate, 5.0%
Octocrylene, 5.0%

Purpose

Sunscreen

Uses

- Helps prevent sunburn
- If used as directed with other sun protection measures (see Directions), decreases the risk of skin cancer and early skin aging caused by the sun

Warnings

For external use only.

Do not use on

- damaged or broken skin.

When using this product

- keep out of eyes. Rinse with water to remove.

Stop use and ask a doctor

- if rash occurs.

Keep Out of Reach of Children.

If swallowed, get medical help or contact a Poison Control Center right away.

Directions

- Apply liberally 15 minutes before sun exposure.
- Children under 6 months of age: ask a doctor
- Reapply at least every 2 hours
- Use water-resistant sunscreen if swimming or sweating
- Sun Protection Measures: Spending time in the sun increases your risk of skin cancer and early skin aging. To decrease this risk, regularly use a sunscreen with a Broad Spectrum SPF value of 15 or higher and other sun protection measures including:
  - limit time in the sun, especially from 10 a.m. - 2 p.m.
  - wear long-sleeved shirts, pants, hats and sunglasses

Other Information

- protect the product in this container from excessive heat and direct sun

Inactive Ingredients

water, cyclohexasiloxane, glycerin, titanium dioxide, glyceryl stearate, PEG-100 stearate, beeswax, myristyl myristate, stearic acid, palmitic acid, polyglyceryl-10 pentastearate, behenyl alcohol, sodium steroyl lactylate, tocopheryl acetate (vitamin E), butylene glycol, carbomer, polysorbate 20, palmitoyl tripeptide-1, palmitoyl tetrapeptide-7, propylene glycol, diazolidinyl urea, methylparaben, propylparaben, cetyl alcohol, stearyl alcohol, hydrolyzed soy protein, dipalmitoyl hydroxyproline, fragrance, triethanolamine, glycine soja (soybean) protein, xanthan gum, retinyl palmitate (vitamin A), phenoxyethanol, PEG-20 stearate, potassium sorbate, sodium benzoate, phenethyl alcohol, alcohol denat., chlorphenesin, alcohol.

Package/Label Principal Display Panel - Carton Label

SHOPKO®

*Compare to active ingredients in L’Oreal® Revitalift® Anti-Wrinkle + Firming Day Cream

Anti-Wrinkle & Firming Moisturizer
Day Cream / SPF 18 Broad Spectrum Sunscreen

with Pro-Vitamin A, Teterapeptide Complex & Sepilift™

NET WT 1.7 OZ (48g)

FIRMING & ANTI-WRINKLE: AN INNOVATIVE TECHNOLOGY
Now experience the advanced actions against the signs of skin aging. New Anti-Wrinkle & Firming Day Cream Broad Spectrum SPF18 Sunscreen, with effective encapsulated Pro-Vitamin A, Tetrapeptide Complex and Sepilift™ will increase cell turnover, reduce wrinkles, firm the skin, and provide 24 hour moisturization.

FORMULA ESSENTIALS

- UV SPF18 sunscreen
- Non-Comedogenic
- Dermatologist tested for gentleness
- Non-greasy

*This product is not manufactured or distributed by L'Oreal®, owner of the registered trademark Revitalift®.

Distributed by Shopko Stores
Operating Co., LLC
700 Pilgrim Way, Green Bay, WI 54307
©2014 Shopko Stores
Operating Co., LLC
www.shopko.com
Manufactured in Israel
37815 8C C1

SHOPKO®
Satisfaction Guaranteed

By Refund or Exchange

TRIPLE-ACTION TECHNOLOGY
Advanced Anti-Wrinkle Action: Encapsulated Pro-Vitamin A and Sepilift™ will hasten skin renewal, reducing the amount of fine lines and wrinkles and their depth. Results can be seen in just two weeks. The new technology will continually act to help fight the signs of aging.

Innovative Firming: Tetrapeptide Complex has proven to show renewed elastin and collagen fiber^+. Skin's surface is remodeled, becoming more resilient and toned.

Continuous Moisturization & Skin Protection: Provides 24 hour moisturization to soothe dry skin. Broad spectrum UVA/UVB SPF18 protects the skin and prevents skin damage by UV exposure.

DIRECTIONS FOR USE: Every day, smooth gently onto face and neck until thoroughly absorbed. Use in the AM, alone or under makeup.

Results: Skin's elasticity is improved, Visible reduction of wrinkles and skin looks smoother, Firmer skin

Sepilift™ is a registered trademark owned by Seppic.

^+ In-vitro testing

Carton Label